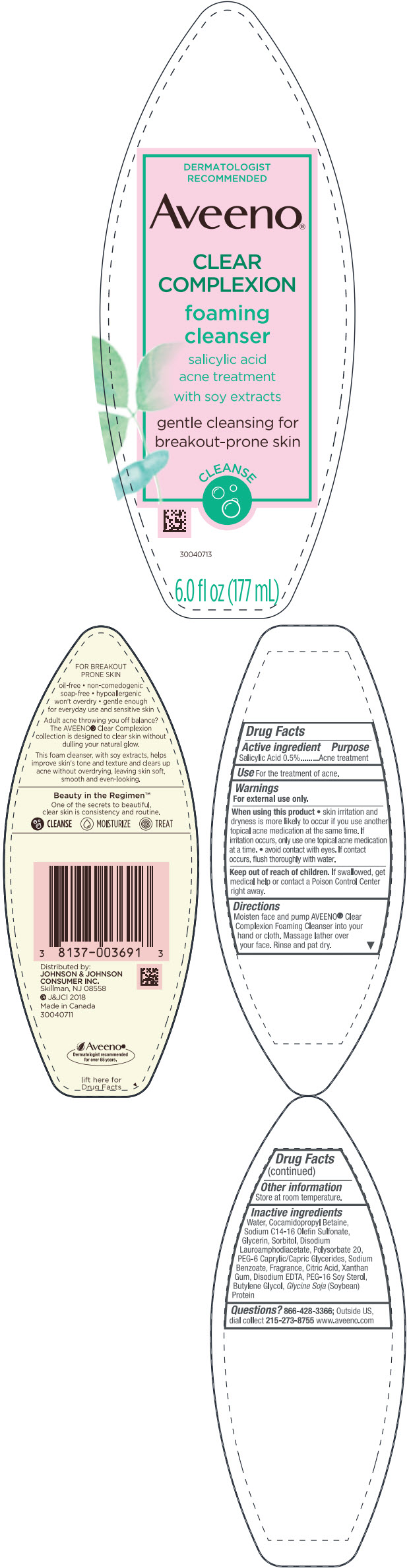 DRUG LABEL: Aveeno CLEAR COMPLEXION foaming cleanser
NDC: 69968-0471 | Form: LIQUID
Manufacturer: Kenvue Brands LLC
Category: otc | Type: HUMAN OTC DRUG LABEL
Date: 20241105

ACTIVE INGREDIENTS: SALICYLIC ACID 5 mg/1 mL
INACTIVE INGREDIENTS: WATER; COCAMIDOPROPYL BETAINE; SODIUM C14-16 OLEFIN SULFONATE; GLYCERIN; SORBITOL; DISODIUM LAUROAMPHODIACETATE; POLYSORBATE 20; PEG-6 CAPRYLIC/CAPRIC GLYCERIDES; SODIUM BENZOATE; CITRIC ACID MONOHYDRATE; XANTHAN GUM; EDETATE DISODIUM ANHYDROUS; PEG-16 SOY STEROL; BUTYLENE GLYCOL; SOYBEAN

Aveeno® CLEAR COMPLEXION foaming cleanser

Drug Facts

Active ingredient

Salicylic Acid 0.5%

Purpose

Acne treatment

Use

For the treatment of acne.

Warnings

For external use only.

When using this product

- skin irritation and dryness is more likely to occur if you use another topical acne medication at the same time. If irritation occurs, only use one topical acne medication at a time.
- avoid contact with eyes. If contact occurs, flush thoroughly with water.

Keep out of reach of children. If swallowed, get medical help or contact a Poison Control Center right away.

Directions

Moisten face and pump AVEENO® Clear Complexion Foaming Cleanser into your hand or cloth. Massage lather over your face. Rinse and pat dry.

Other information

Store at room temperature.

Inactive ingredients

Water, Cocamidopropyl Betaine, Sodium C14-16 Olefin Sulfonate, Glycerin, Sorbitol, Disodium Lauroamphodiacetate, Polysorbate 20, PEG-6 Caprylic/Capric Glycerides, Sodium Benzoate, Fragrance, Citric Acid, Xanthan Gum, Disodium EDTA, PEG-16 Soy Sterol, Butylene Glycol, Glycine Soja (Soybean) Protein

Questions?

866-428-3366; Outside US, dial collect 215-273-8755 www.aveeno.com

Distributed by:
JOHNSON & JOHNSON
CONSUMER INC.
Skillman, NJ 08558

PRINCIPAL DISPLAY PANEL - 177 mL Bottle Label

DERMATOLOGIST
RECOMMENDED
Aveeno®
CLEAR
COMPLEXION
foaming
cleanser
salicylic acid
acne treatment
with soy extracts
gentle cleansing for
breakout-prone skin
CLEANSE

6.0 fl oz (177 mL)